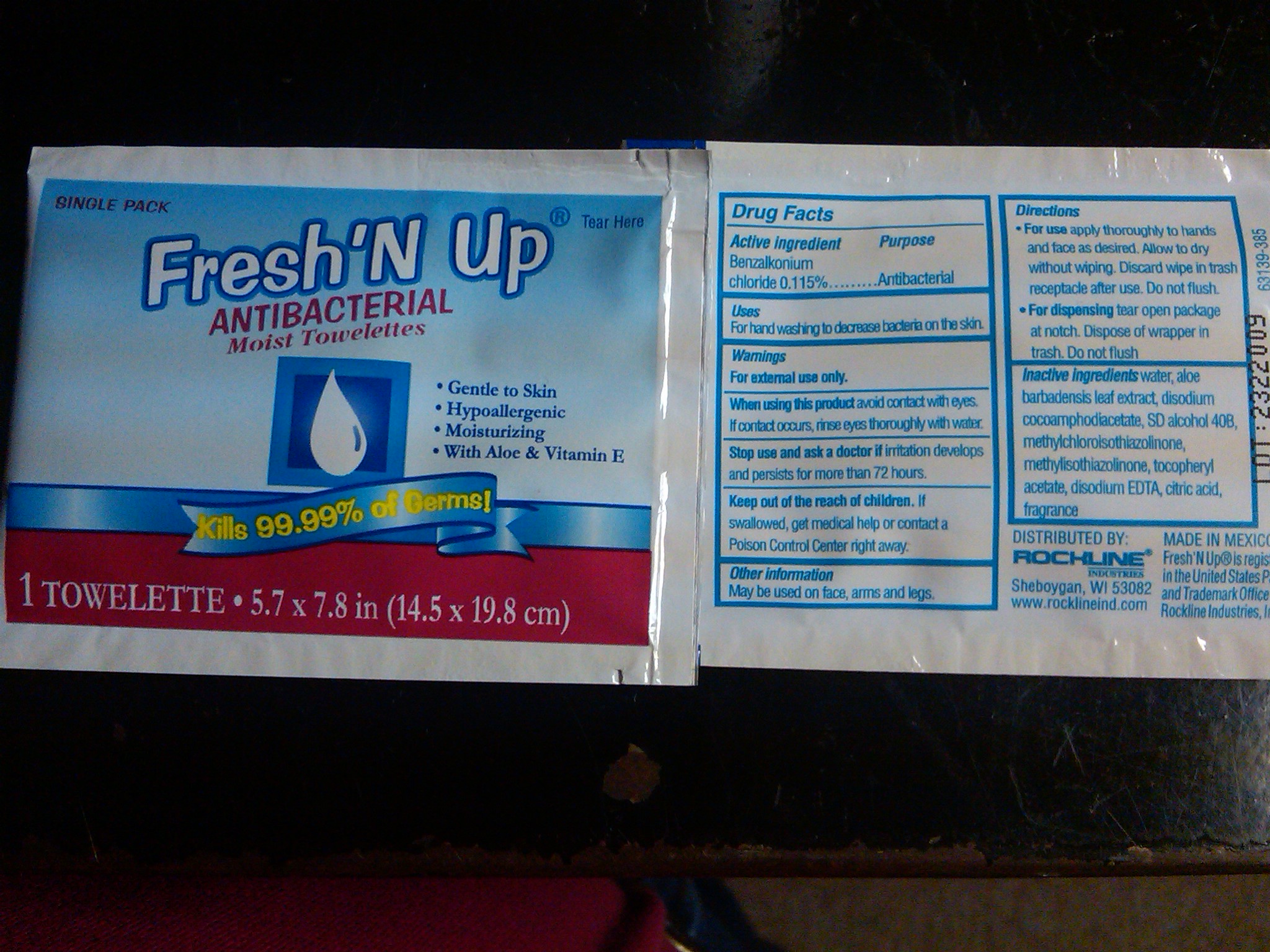 DRUG LABEL: Fresh N Up
NDC: 57624-601 | Form: SOLUTION
Manufacturer: Rockline Industries, Inc
Category: otc | Type: HUMAN OTC DRUG LABEL
Date: 20100921

ACTIVE INGREDIENTS: BENZALKONIUM CHLORIDE 0.115 mL/100 mL
INACTIVE INGREDIENTS: WATER; ALOE VERA LEAF; METHYLCHLOROISOTHIAZOLINONE; METHYLISOTHIAZOLINONE; EDETATE DISODIUM; CITRIC ACID MONOHYDRATE

Drug Facts

Active Ingredient

Benzalkonium chloride 0.115%

Purpose

Antibacterial

Uses

For hand washing to decrease bacteria on the skin

Warnings

For external use only

When using this product

avoid the eyes and mucous membranes
If contact occurs, rinse eyes thoroughly with water

Stop use and ask a doctor if

if irritation develops and persists for more than 72 hours.

Keep out of reach of children. If swallowed contact a doctor or Poison Control Center right away.

Other Information

May be used on face, arms and legs.

Directions

- For use apply thoroughly to hands and face as desired. Allow to dry without wiping. Discard wipe in trash receptacle after use. Do not flush.
- For dispensing tear open package at notch. Dispose of wrapper in trash. Do not flush

Inactive Ingredients

Acrylates Copolymer, Benzophenone-4, Citric Acid, Cocamide DEA, Cocamidopropyl Betaine, Disodium EDTA, FDC Yellow 5, FDC Blue 1, Fragrance, Methylchloroisothiazolinone, Methylisothiazolinone, Sodium Chloride, Sodium Laureth Sulfate, Water

Package Label